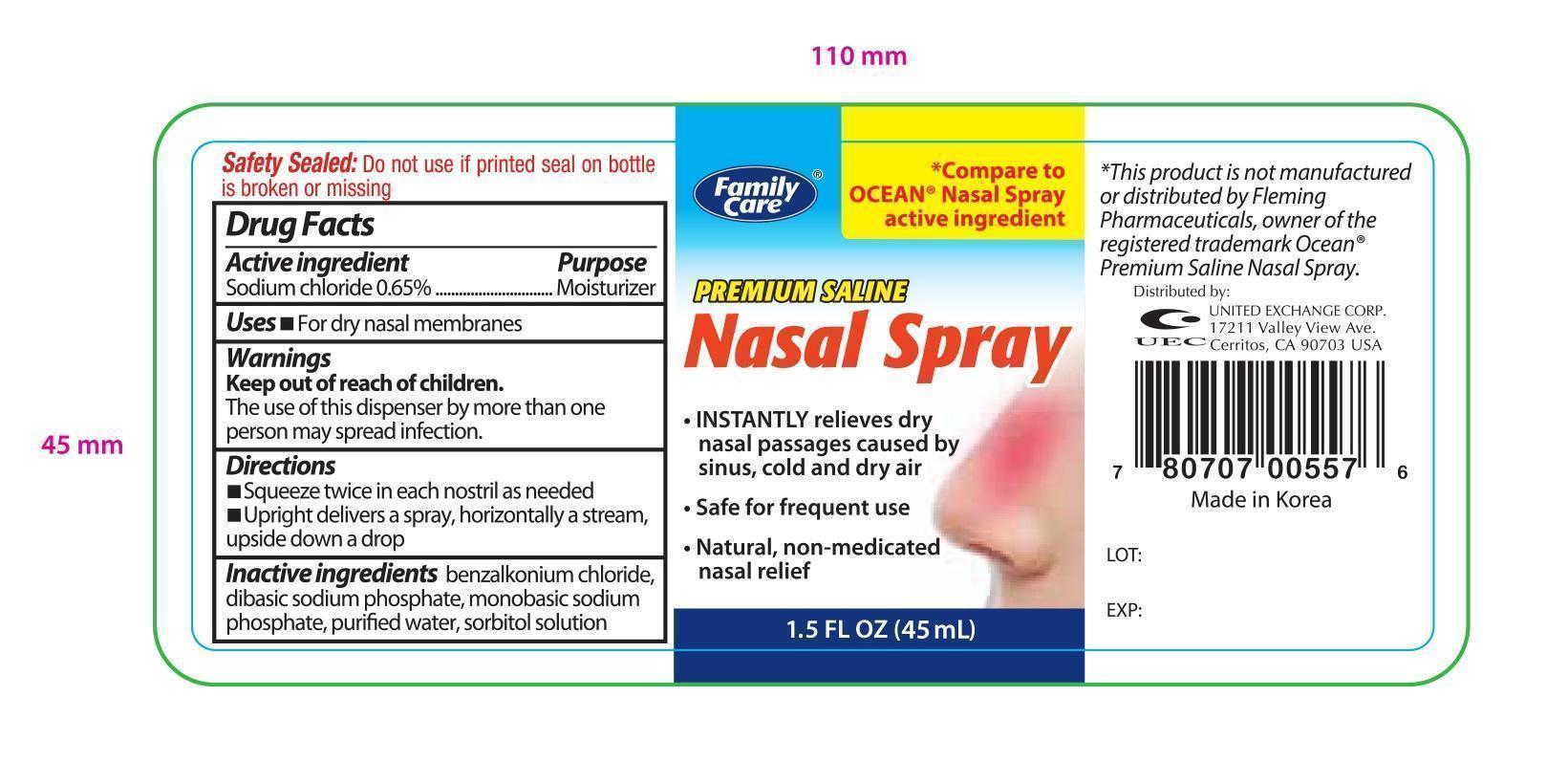 DRUG LABEL: Family Care Premium Saline Nasal 
NDC: 65923-557 | Form: SOLUTION
Manufacturer: United Exchange Corp
Category: otc | Type: HUMAN OTC DRUG LABEL
Date: 20140602

ACTIVE INGREDIENTS: SODIUM CHLORIDE 0.29 mg/44 mL
INACTIVE INGREDIENTS: BENZALKONIUM CHLORIDE; SODIUM PHOSPHATE, DIBASIC; SODIUM PHOSPHATE, MONOBASIC; WATER; SORBITOL

Drug Facts

Active Ingredient Purpose

Sodium chloride 0.65%................................Moisturizer

Uses

- For dry nasal membranes

Warnings

For external use only

Keep out of reach of children

DO NOT USE

The use of this dispenser by more than one person may spread infection

Directions

- squeeze twice in each nostril as needed
- upright delivers a spray, horizontally a stream, upside down a drop

Inactive Ingredeints

Benzalkonium chloride, dibasic sodium phosphate, monobasic sodium, phosphate, purified water, sorbitol solution

DOSAGE AND ADMINISTRATION

Distributed by:

United Exchange Corp.

17211 Valley View Ave.

Cerritos, CA 90703 USA